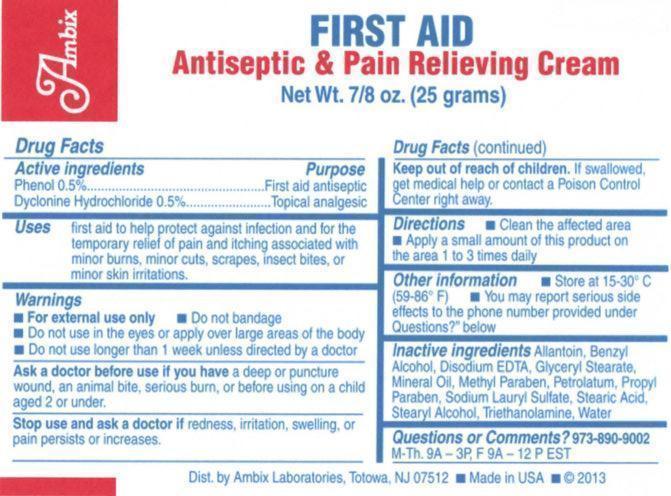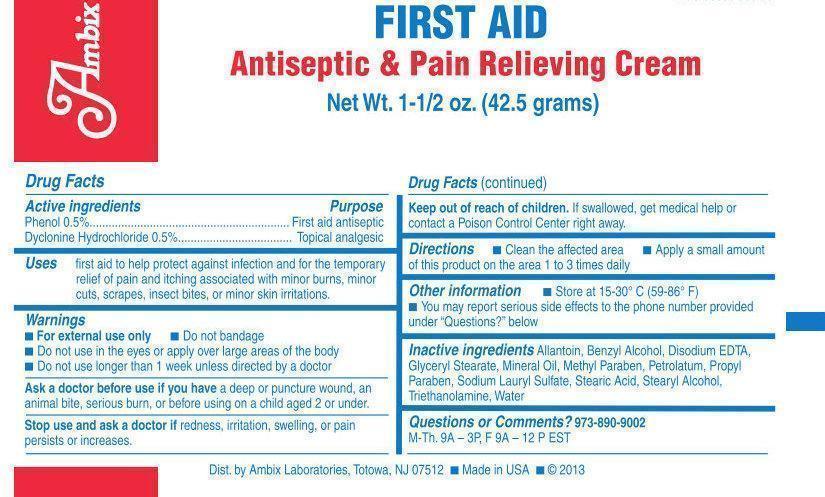 DRUG LABEL: Ambix First Aid
NDC: 10038-250 | Form: CREAM
Manufacturer: Organics Corporation of America dba Ambix Laboratories
Category: otc | Type: HUMAN OTC DRUG LABEL
Date: 20191104

ACTIVE INGREDIENTS: DYCLONINE HYDROCHLORIDE 0.005 g/1 g; PHENOL 0.005 g/1 g
INACTIVE INGREDIENTS: ALLANTOIN; BENZYL ALCOHOL; EDETATE DISODIUM; GLYCERYL MONOSTEARATE; MINERAL OIL; METHYLPARABEN; PETROLATUM; PROPYLPARABEN; SODIUM LAURYL SULFATE; STEARIC ACID; STEARYL ALCOHOL; TROLAMINE; WATER

Ambix First Aid Antiseptic & Pain Relieving Cream

Active Ingredients

Phenol 0.5%

Dyclonine Hydrochloride 0.5%

Purpose

First Aid Antiseptic

Topical Anesthetic

Uses

- first aid to help protect against infection and for the temporary relief of pain and itching associated with minor burns, minor cuts, scrapes, insect bites, or minor skin irritations.

Warnings

■ For external use only ■ Do not bandage ■ Do not use in the eyes or apply over large areas of the body ■ Do not use longer than 1 week unless directed by a doctor

Do not use in eyes, do not apply over large areas of the body. In case of deep puncture wounds or serious burns, consult a doctor.

Ask a doctor before use if you have

a deep or puncture wound, an animal bite, serious burn, or before using on a child aged 2 or under.

Stop use and ask a doctor if

redness, irritation, swelling, or pain persists or increases.

Keep out of reach of children

If swallowed, get medical help or contact a Poison Control Center right away.

Directions

■ Clean the affected area ■ Apply a small amount of this product on the area 1 to 3 times daily

Other Information

- Store at controlled room temperature 15ºC to 30ºC (59ºF to 86ºF).
- You may report serious side effects to the phone number provided under “Questions?” below

Inactive Ingredients

Allantoin, Benzyl Alcohol, Disodium EDTA, Glyceryl Stearate, Mineral Oil, Methyl Paraben, Petrolatum, Propyl Paraben, Sodium Lauryl Sulfate, Stearic Acid, Stearyl Alcohol, Triethanolamine, Water

PACKAGE LABEL

Ambix

FIRST AID

Antiseptic & Pain Relieving Cream

Net Wt. 7/8 oz. (25 grams)

Dist. by Ambix Laboratories, Totowa, NJ 07512 ■ Made in USA ■ © 2013

Ambix

FIRST AID

Antiseptic & Pain Relieving Cream

Net Wt. 1-1/2 oz. (42.5 grams)

Dist. by Ambix Laboratories, Totowa, NJ 07512 ■ Made in USA ■ © 2013